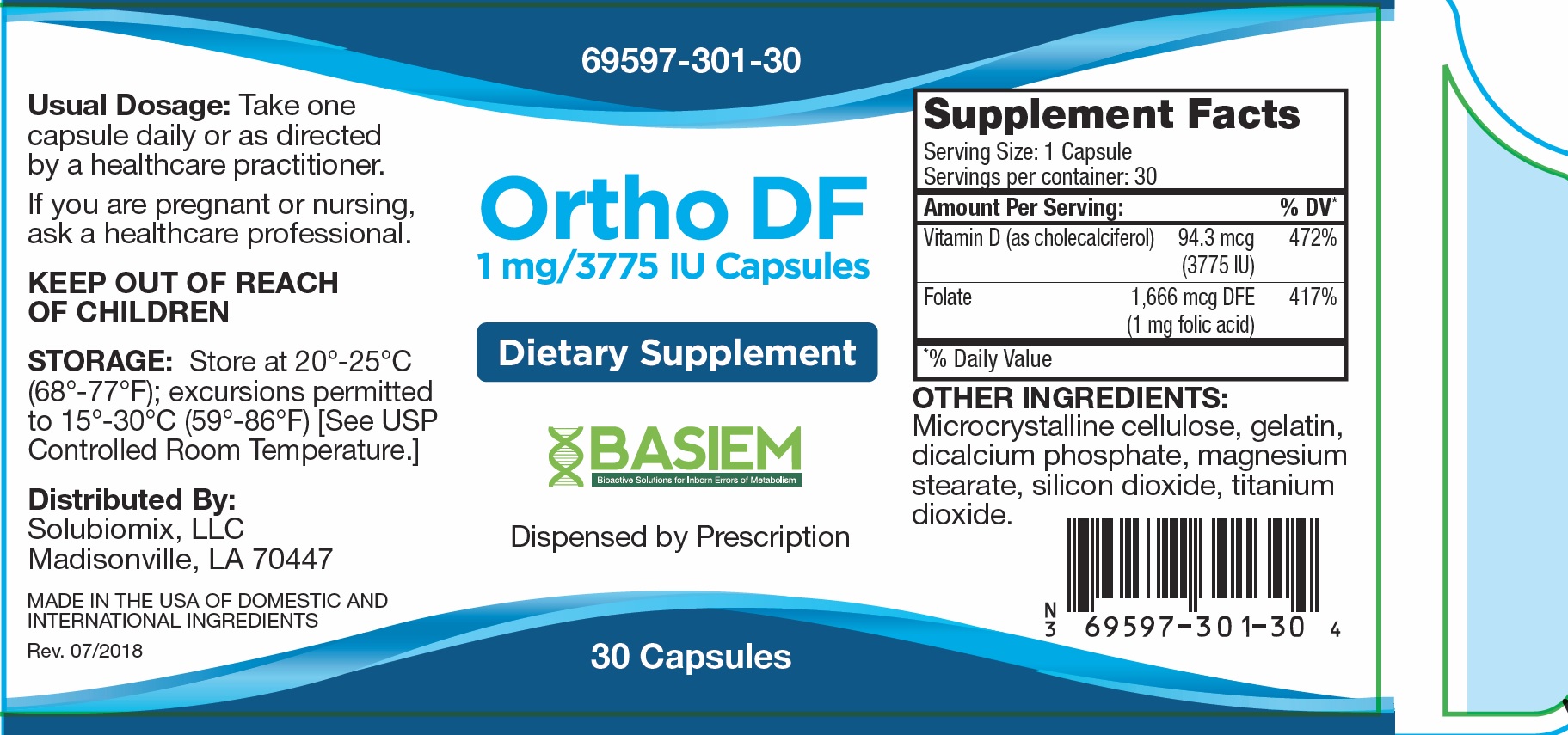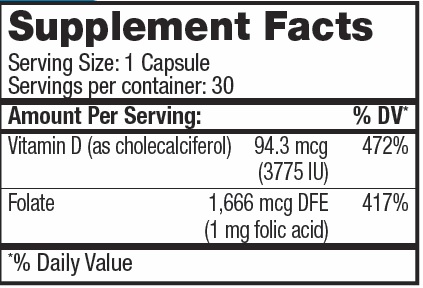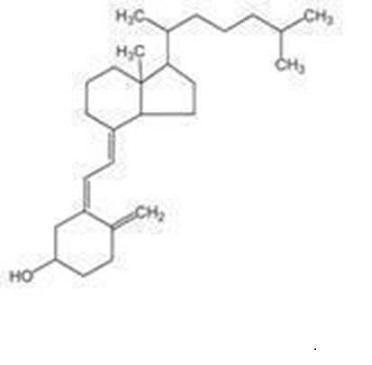 DRUG LABEL: Ortho DF
NDC: 69597-301 | Form: CAPSULE
Manufacturer: Basiem
Category: other | Type: DIETARY SUPPLEMENT
Date: 20251006

ACTIVE INGREDIENTS: FOLIC ACID 1 mg/1 mg; VITAMIN D .094 mg/1 mg
INACTIVE INGREDIENTS: GELATIN; CELLULOSE ACETATE; MAGNESIUM STEARATE; SILICON DIOXIDE

Ortho DF

STATEMENT OF IDENTITY

Ortho DF Capsules is an orally administered prescription folate product for the dietary management of patients with unique nutritional needs requiring increased folate levels and Vitamin D supplementation due to Vitamin D deficiency and other nutritional supplementation.
Ortho DF should be administered under the supervision of a licensed medical practitioner.

Vitamin D3 (cholecalciferol) is a white, crystalline powder, very soluble in water, with the following structural formula:

Each capsule contains:
Folic Acid .......................................................................1,666 mcg DFE (1 mg)
Vitamin D3 (Cholecalciferol) .............................................94.3 mcg (3775 IU)

Each capsule contains the following inactive ingredients: Gelatin, cellulose, magnesium stearate, silica.

The in vivo synthesis of the major biologically active metabolites of vitamin D occurs in two steps. The first hydroxylation of ergocalciferol takes place in the liver (to 25-hydroxyvitamin D) and the second in the kidneys (to 1,25-dihydroxyvitamin D). Vitamin D metabolites promote the active absorption of calcium and phosphorus by the small intestine, thus elevating serum calcium and phosphate levels sufficiently to permit bone mineralization. Vitamin D metabolites also mobilize calcium and phosphate from bone and probably increase the reabsorption of calcium and perhaps also of phosphate by the renal tubules.

There is a time lag of 10 to 24 hours between the administration of vitamin D and the initiation of its action in the body due to the necessity of synthesis of the active metabolites in the liver and kidneys. Parathyroid hormone is responsible for the regulation of this metabolism in the kidneys.

HEALTH CLAIM:

Ortho DF is used for dietary management of patients with unique nutritional needs requiring increased folate levels, Vitamin D deficiency or are in need of Vitamin D supplementation and other nutritional supplementation.

Ortho DF can be taken by women of childbearing age, pregnant women, and lactating and nonlactating mothers.

PRECAUTIONS:

KEEP OUT OF THE REACH OF CHILDREN.

Tell your doctor if you have: kidney problems, thyroid disease. This medication should be used as directed during pregnancy or while breast-feeding. Consult your doctor about the risks and benefits.

Folic acid alone is improper therapy in the treatment of pernicious anemia and other megaloblastic anemias where vitamin B12 is deficient. Folic acid in doses above 0.1 mg daily may obscure pernicious anemia in that hematologic remission can occur while neurological manifestations progress.

WARNINGS SECTION

Allergic sensitization has been reported following both oral and parenteral administration of folic acid.
You should call your doctor for medical advice about serious adverse events. To report adverse side effects or to obtain product information, contact Solubiomix, LLC, at 1-844-551-9911.

DOSAGE AND ADMINISTRATION:

Take one or two capsules daily or as directed by a healthcare practitioner.

PACKAGE LABEL

KEEP OUT OF THE REACH OF CHILDREN.

Store at 20°-25°C (68°-77°F); excursions permitted to 15°-30°C (59°-86°F) [See USP Controlled Room Temperature.]
Protect from heat, light and moisture.

Tamper Evident: Do not use if seal is broken or missing

Ortho DF capsules are supplied as clear capsules printed with “301” dispensed in child-resistant bottles of 30ct (69597-301-30*).

* This product is a prescription-folate with or without other dietary ingredients that – due to increased folate levels (AUG 2 1973 FR 20750), requires an Rx on the label because of increased risk associated with masking of B12 deficiency (pernicious anemia). Based on our assessment of the risk of obscuring pernicious anemia, this product requires licensed medical supervision, an Rx status, and a National Drug Code (NDC) – or similarly-formatted product code, as required by pedigree reporting requirements and supply-chain control as well as – in some cases, for insurance-reimbursement applications.
All prescriptions using this product shall be pursuant to state statutes as applicable. This is not an Orange Book product. This product may be administered only under a physician’s supervision. There are no implied or explicit claims on therapeutic equivalence.